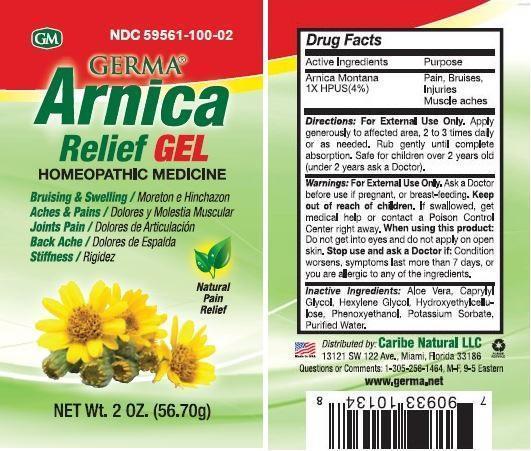 DRUG LABEL: Germa Arnica Relief
NDC: 59561-100 | Form: GEL
Manufacturer: Caribe Natural LLC
Category: homeopathic | Type: HUMAN OTC DRUG LABEL
Date: 20150624

ACTIVE INGREDIENTS: ARNICA MONTANA 1 [hp_X]/100 g
INACTIVE INGREDIENTS: ALOE VERA LEAF; CAPRYLYL GLYCOL; HEXYLENE GLYCOL; HYDROXYETHYL CELLULOSE (100 MPA.S AT 2%); PHENOXYETHANOL; POTASSIUM SORBATE; WATER

Active Ingredients Purpose

Arnica Montana 1X HPUS (4%) Pain, Bruises, Injuries, Muscle Aches

PURPOSE

Pain, Bruises, Inuries, Muscle Aches

Keep out of reach of children. If swallowed, get medical help or contact a Poison Control Center right away.

INDICATIONS AND USAGE

Germa Arnica Relief Gel

Homeopathic Medicine

Bruising & Swelling / Moreton e Hinchazon

Aches & Pains / Dolores y Molestia Muscular

Joints Pain / Dolores de Articulacion

Back Ache / Dolores de Espalda

Stiffness / Rigidez

Natural Pain Relief

Directions:

For External Use Only. Apply generously to affected area, 2 to 3 times daily or as needed. Rub gently until complete absorption. Safe for children over 2 years old (under 2 years ask a Doctor).

Warnings:

For External Use Only. Ask a Doctor before use if pregnant, or breast-feeding. When using this product: Do not get into eyes and do not apply on open skin. Stop use and ask a Doctor if: Condition worsens, symptoms last more than 7 days, or you are allergic to any of the ingredients.

INACTIVE INGREDIENT

Inactive Ingredients: aloe vera, caprylyl glycol, hexylene glycol, hydroxyethylcellulose, phenoxyethanol, potassium sorbate, purified water.